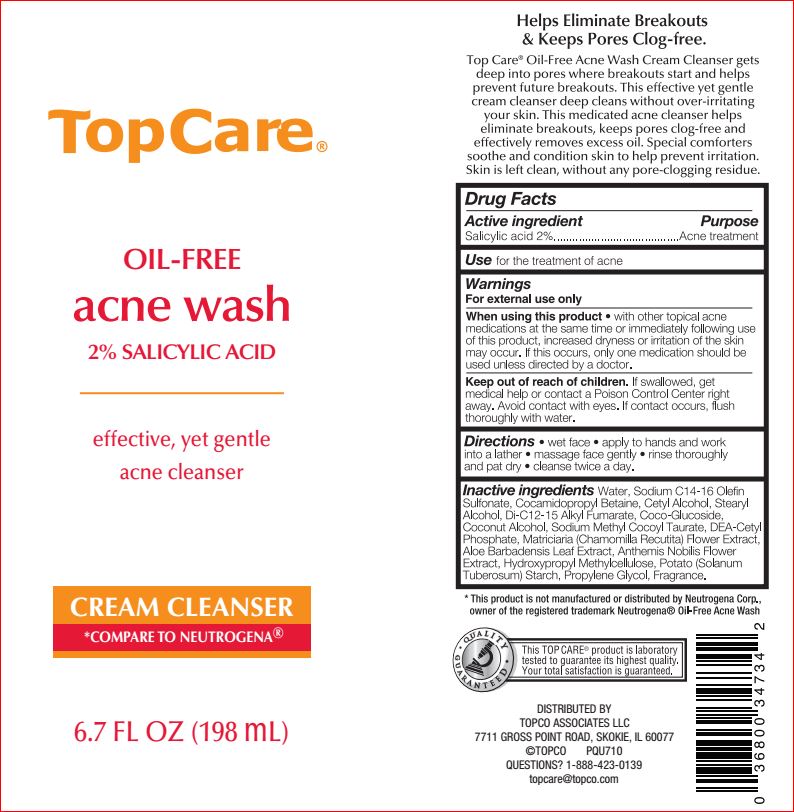 DRUG LABEL: Oil Free Acne Wash
NDC: 36800-743 | Form: CREAM
Manufacturer: Topco
Category: otc | Type: HUMAN OTC DRUG LABEL
Date: 20180725

ACTIVE INGREDIENTS: Salicylic Acid 2 g/100 mL
INACTIVE INGREDIENTS: Water; Sodium C14-16 Olefin Sulfonate; Cocamidopropyl Betaine; Cetyl Alcohol; Stearyl Alcohol; Di-C12-15 Alkyl Fumarate; COCO GLUCOSIDE; Coconut Alcohol; Sodium Methyl Cocoyl Taurate; DIETHANOLAMINE CETYL PHOSPHATE; CHAMOMILE; ALOE VERA LEAF; CHAMAEMELUM NOBILE FLOWER; HYPROMELLOSES; STARCH, POTATO; Propylene Glycol

Drug Facts

Active ingredient Purpose

Salicylic acid 2%..................... Acne treatment

INDICATIONS AND USAGE

Use for the treatment of acne

Warnings For external use only

When using other topical acne medications at the same time or immediately following use of this product. This may increase dryness or irritation of the skin. If this occurs, only one medication should be used unless directed by a doctor

Keep out of reach of children. If swallowed, get medical help or contact a Poison Control Center right away. Avoid contact with eyes. If contact occurs, flush thoroughly with water.

DOSAGE AND ADMINISTRATION

Directions • wet face • apply to hands and work into a lather • massage face gently • rinse thoroughly and pat dry • cleanse twice a day.

INACTIVE INGREDIENT

Inactive ingredients: Water, Sodium C14-16 Olefin Sulfonate, Cocamidopropyl Betaine, Cetyl Alcohol, Stearyl Alcohol, Di-C12-15 Alkyl Fumarate, Coco-Glucoside, Coconut Alcohol, Sodium Methyl Cocoyl Taurate, DEA-Cetyl Phosphate, Matriciaria (Chamomilla Recutita) Flower Extract, Aloe Barbadensis Leaf Extract, Anthemis Nobilis Flower Extract, Hydroxypropyl Methylcellulose, Potato (Solanum Tuberosum) Starch, Propylene Glycol, Fragrance.